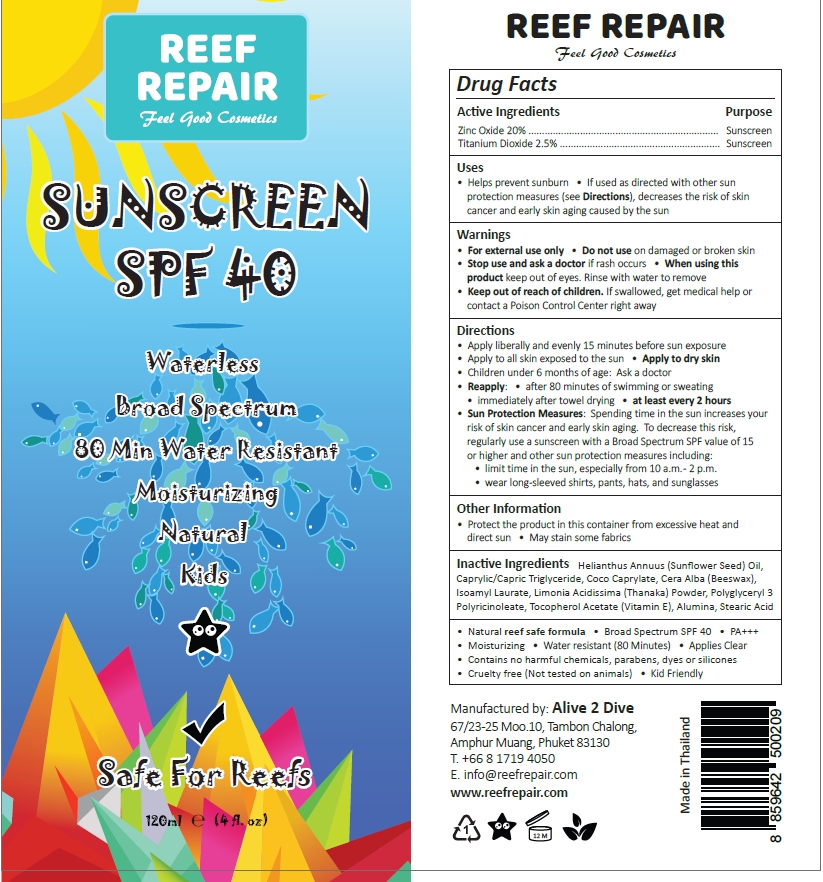 DRUG LABEL: Reef Repair Sunscreen SPF 40
NDC: 73541-003 | Form: CREAM
Manufacturer: Alive 2 Dive Co Ltd
Category: otc | Type: HUMAN OTC DRUG LABEL
Date: 20240517

ACTIVE INGREDIENTS: TITANIUM DIOXIDE 2.5 g/100 mL; ZINC OXIDE 20 g/100 mL
INACTIVE INGREDIENTS: SUNFLOWER OIL; .ALPHA.-TOCOPHEROL ACETATE; POLYGLYCERYL-3 PENTARICINOLEATE; MEDIUM-CHAIN TRIGLYCERIDES; COCO-CAPRYLATE; YELLOW WAX; LIMONIA ACIDISSIMA WHOLE; ALUMINUM OXIDE; ISOAMYL LAURATE; STEARIC ACID

Reef Repair Sunscreen SPF 40

Active ingredients

Zinc oxide 20%

Titanium dioxide 2.5%

Purpose

Sunscreen

Uses

- helps prevent sunburn
- if used as directed with other sun protection measures (see Directions), decreases the risk of skin cancer and early skin aging caused by the sun

Warnings

For external use only

Do not use on damaged or broken skin

Stop use and ask a doctor if rash occurs

when using this product keep out of eyes. Rinse with water to remove

Keep out of reach of children. If swallowed, get medical help or contact a Poison Control Center right away.

Directions

- Apply liberally and evenly 15 minutes before sun exposure
- Apply to all skin exposed to the sun
- Apply to dry skin
- Children under 6 months of age: Ask a doctor
- Reapply: after 80 minutes of swimming or sweating; immediately after towel drying; at least every 2 hours
- Sun Protection Measures: Spending time in the sun increases your rish of skin cancer and early skin aging. To decrease this risk, regularly use a suncreen with a Broad Spectrum SPF value of 15 or higher and other sun protection measures including:
- limit time in the sun, especially from 10 a.m-2 p.m.
- wear long-sleeved shirts, pants, hats, and sunglasses.

Other information

- Protect the product in this container from excessive heat and direct sun
- May stain some fabrics

Inactive ingredients

Helianthus annuus (Sunflower seed) oil

Caprylic/Capric Triglyceride

Coco Caprylate

Cera alba (Beeswax)

Isoamyl Laurate

Limonia Acidissim (Thanaka) powder

Polyglyceryl 3 Polyricinoleate

Tocopherol Acetate (Vitamin E)

Stearic acid

Alumina

QUESTIONS

- Natural reef safe formula
- Broad Spectrum SPF 40
- PA+++
- Moisturizing
- Water resistant (80 Minutes)
- Applies Clear
- Contains no harmful chemicals, parabens, dyes or silicones
- Cruelty free (Not tested on animals)
- Kid Friendly